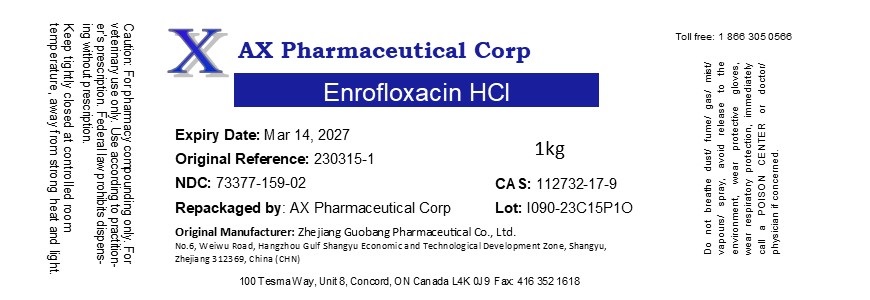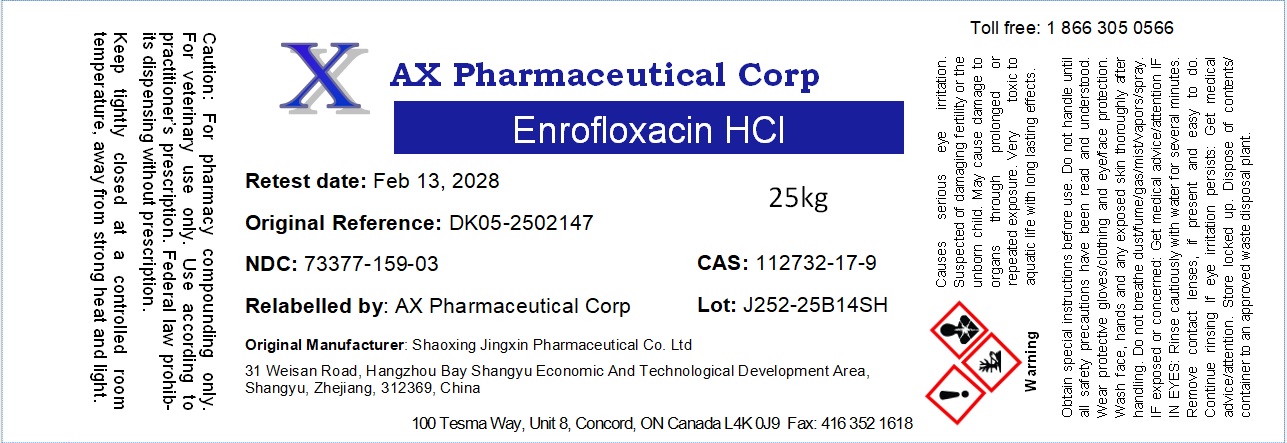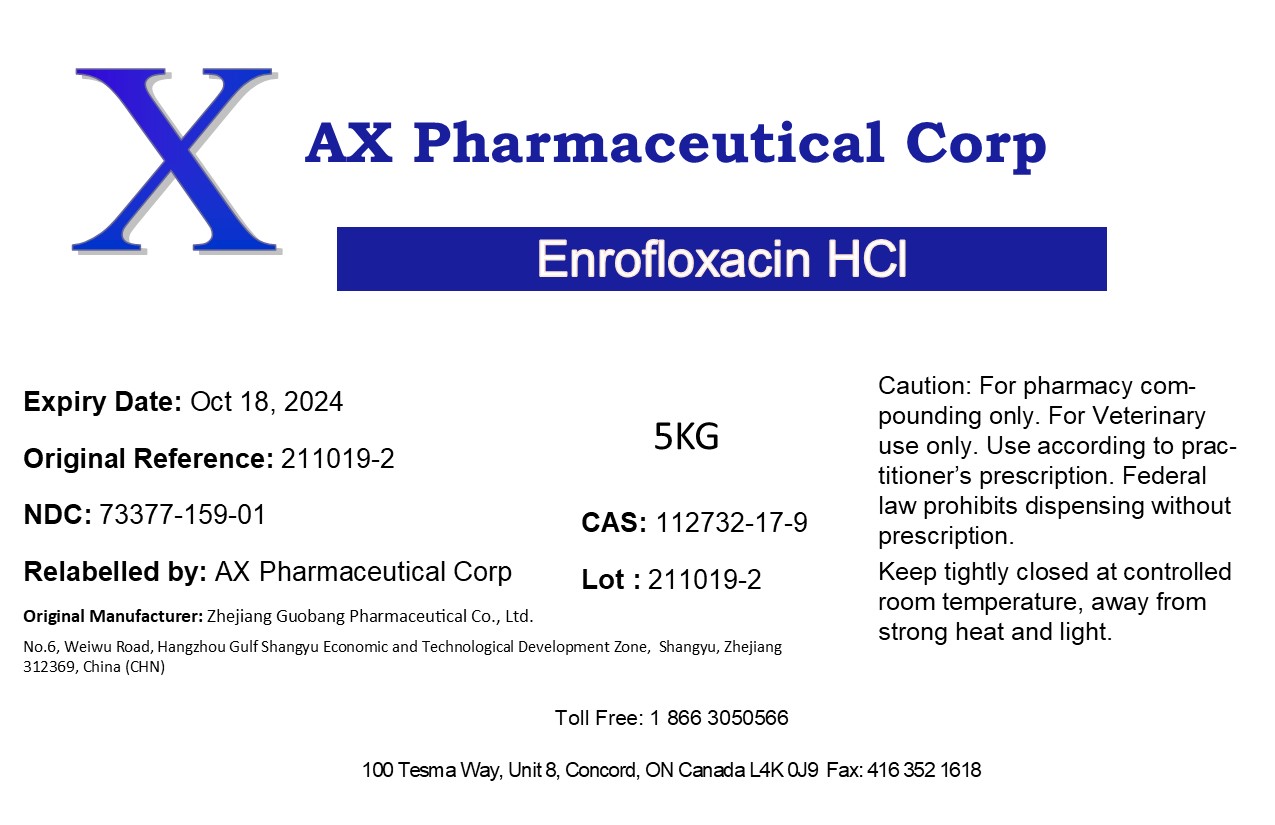 DRUG LABEL: Enrofloxacin HCl
NDC: 73377-159 | Form: POWDER
Manufacturer: AX Pharmaceutical Corp
Category: other | Type: BULK INGREDIENT - ANIMAL DRUG
Date: 20260119

ACTIVE INGREDIENTS: ENROFLOXACIN 1 kg/1 kg

Enrofloxacin HCl